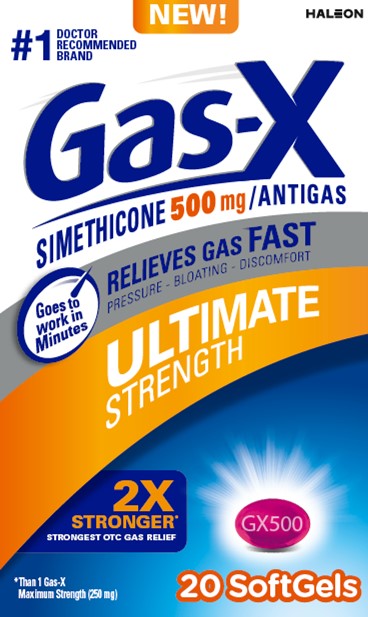 DRUG LABEL: Gas-X

NDC: 0067-8075 | Form: CAPSULE, LIQUID FILLED
Manufacturer: Haleon US Holdings LLC
Category: otc | Type: HUMAN OTC DRUG LABEL
Date: 20250520

ACTIVE INGREDIENTS: DIMETHICONE, UNSPECIFIED 500 mg/1 1
INACTIVE INGREDIENTS: D&C RED NO. 27 ALUMINUM LAKE; GELATIN, UNSPECIFIED; GLYCERIN; MEDIUM-CHAIN TRIGLYCERIDES; WATER; SOYBEAN LECITHIN

Drug Facts

Active ingredient (in each softgel)

Simethicone 500 mg

Purpose

Antigas

Use

for the relief of

- pressure, bloating, and fullness commonly referred to as gas

Directions

- adults and children 12 years and older: swallow with water 1 softgel after meals or at bedtime
- do not exceed 1 softgel in 24 hours except under the advice and supervision of a physician

Other information

- store at controlled room temperature 20-25ºC (68-77ºF)
- protect from light, heat and moisture

Inactive ingredients

D&C red no. 27 aluminum lake, gelatin, glycerin, medium-chain triglycerides, pharmaceutical ink, purified water, soy lecithin

Questions or comments?

1-800-452-0051

Additional information

Gas-XUltimate Strength
Softgels offer fast, effective relief of pressure and bloating. They are specially formulated with simethicone, the antigas medicine doctors recommend most for pressure, bloating, or discomfort referred to as gas.

READ ALL PRODUCT INFORMATION BEFORE USING.
KEEP CARTON FOR IMPORTANT INFORMATION.

Gas-XUltimate Strength Softgels contain liquid gas-fighting medicine in a softgels so they are easy to swallow.

TAMPER EVIDENT FEATURE:
Do not use if blister is broken or damaged.

1-800-452-0051

Dist. By: Haleon, Warren, NJ 07059

Trademarks owned or licensed by Haleon.

©2025 Haleon or licensor.

Principal Display Panel

NEW!

HALEON

#1 DOCTOR RECOMMENDED BRAND

Gas-X

SIMETHICONE 500 mg / ANTIGAS

Goes to work in Minutes

RELIEVES GAS FAST

PRESSURE – BLOATING – DISCOMFORT

ULTIMATE STRENGTH

2X STRONGER*
STRONGEST OTC GAS RELIEF

*Than 1 Gas-X

Maximum Strength (250 mg)

GX500

20 SoftGels